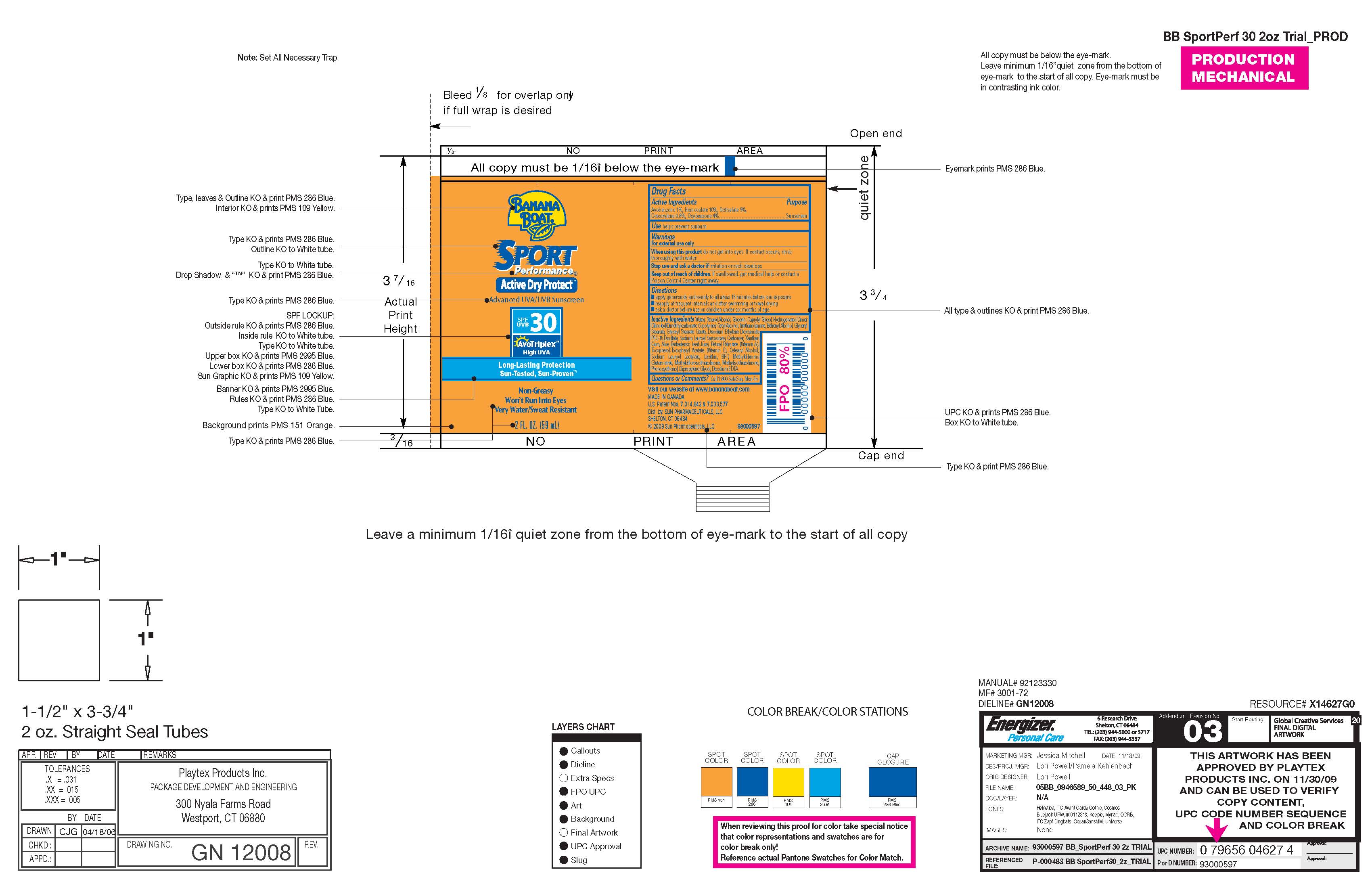 DRUG LABEL: Banana Boat Sport Performance
NDC: 61047-820 | Form: LOTION
Manufacturer: KIK Custom Products
Category: otc | Type: HUMAN OTC DRUG LABEL
Date: 20100325

ACTIVE INGREDIENTS: Avobenzone 0.59 mL/59 mL; Homosalate 5.9 mL/59 mL; Octisalate 2.95 mL/59 mL; Octocrylene 0.47 mL/59 mL; Oxybenzone 2.36 mL/236 mL

Banana Boat Sport Performance Active Dry Protect Advanced UVA/UVB Sunscreen -Long Lasting Protection, Sun Tested, Sun Proven

Drug Facts:
Avobenzone: 1%
Homosalate: 10%
Octisalate: 5%
Octicrylene: 0.8%
Oxybenzone: 4%
Purpose: Sunscreen

WARNINGS

FOR EXTERNAL USE ONLY.
WHEN USING THIS PRODUCT, DO NOT GET INTO EYES IF CONTACT OCCURS, RINSE THOROUGHLY WITH WATER.
STOP USE AND ASK DOCTOR IF IRRITATION OR RASH DEVELOPS. KEEP OUT OF REACH OF CHILDREN.
IF SWALLOWED, GET MEDICAL HELP OR CONTACT POISON CONTROL CENTER RIGHT AWAY.

INACTIVE INGREDIENT

Water, Cetearyl Alcohol, Glycerin, Capryly Glycol, Hydrogenated Dimer Dilnoleyl/Dimethyl Carbonate,
Copolymer, Cetyl Alcohol, Triethanolamine, Behenyl Acohol, Glyceryl Stearate, Glyceryl Stearate, Citrate,
Disodium Ethylene, Dicocamide PEG-15 Disulfate, Sodium Lauroyl Sarcosinate, Carbomer, Xanthan Gum,
Aloe Barbadensis Leaf Juice, Retinyl Palmitate (Vitamin A), Tocopherol, Tocopheryl Acetate (Vitamin E),
Cetearyl Alchol, Sodium Lauroyl, Lactylate, Lecithin, BHT, Methyl Dibromo Glutaronitrile, Methyl Chloisothiazolinone.
Methyl Isothiazolinone, Phenoxy Ethanol, Dipropylene Glycol, Disodium EDTA

Questions or Comments: Call 1-800-SAFESUN Mon-Fri.